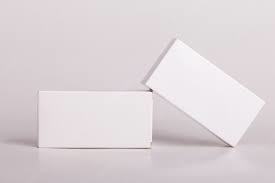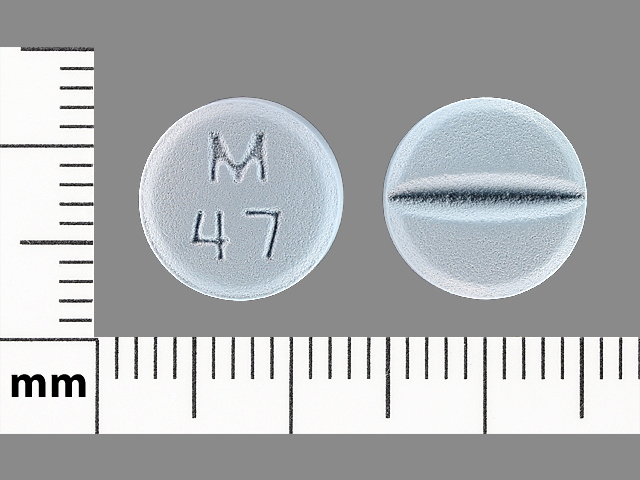 DRUG LABEL: Truemed Group LLC
NDC: 82922-037 | Form: TABLET
Manufacturer: Truemed Group LLC
Category: prescription | Type: HUMAN PRESCRIPTION DRUG LABEL
Date: 20220811

ACTIVE INGREDIENTS: HYDROCHLOROTHIAZIDE 12.5 mg/1 1; TELMISARTAN 80 mg/1 1

TELMISARTAN HYDROCHLOROTHIAZIDE